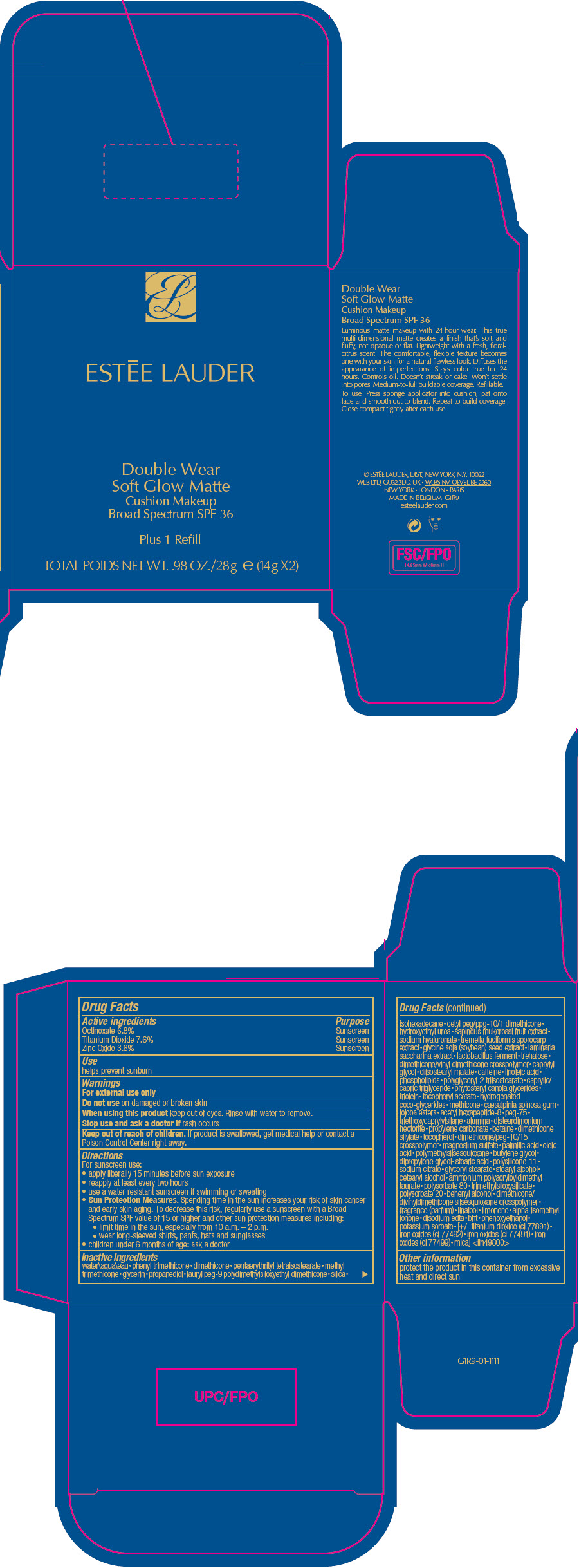 DRUG LABEL: ESTEE LAUDER DOUBLE WEAR SOFT GLOW MATTE CUSHION MAKEUP BROAD SPECTRUM SPF 36
NDC: 11559-062 | Form: GEL
Manufacturer: ESTEE LAUDER INC
Category: otc | Type: HUMAN OTC DRUG LABEL
Date: 20231221

ACTIVE INGREDIENTS: OCTINOXATE 68 mg/1 g; TITANIUM DIOXIDE 76 mg/1 g; ZINC OXIDE 36 mg/1 g
INACTIVE INGREDIENTS: MEDIUM-CHAIN TRIGLYCERIDES; CANOLA OIL; GLYCERYL TRIOLEATE; .ALPHA.-TOCOPHEROL ACETATE; HYDROGENATED COCO-GLYCERIDES; METHICONE (20 CST); CAESALPINIA SPINOSA RESIN; POTASSIUM HYDROLYZED JOJOBA ESTERS; ACETYL HEXAPEPTIDE-8; PEG-75 DILAURATE; TRIETHOXYCAPRYLYLSILANE; ALUMINUM OXIDE; DISTEARDIMONIUM HECTORITE; PROPYLENE CARBONATE; BETAINE; SILICA DIMETHYL SILYLATE; TOCOPHEROL; DIMETHICONE/PEG-10/15 CROSSPOLYMER; MAGNESIUM SULFATE, UNSPECIFIED FORM; PALMITIC ACID; OLEIC ACID; POLYMETHYLSILSESQUIOXANE (11 MICRONS); BUTYLENE GLYCOL; DIPROPYLENE GLYCOL; STEARIC ACID; DIMETHICONE/VINYL DIMETHICONE CROSSPOLYMER (SOFT PARTICLE); SODIUM CITRATE, UNSPECIFIED FORM; GLYCERYL STEARATE SE; STEARYL ALCOHOL; CETOSTEARYL ALCOHOL; AMMONIUM POLYACRYLOYLDIMETHYL TAURATE (55000 MPA.S); POLYSORBATE 80; TRIMETHYLSILOXYSILICATE (M/Q 0.6-0.8); POLYSORBATE 20; DOCOSANOL; DIMETHICONE/DIVINYLDIMETHICONE/SILSESQUIOXANE CROSSPOLYMER; FRAGRANCE CLEAN ORC0600327; LINALOOL, (+)-; LIMONENE, (+)-; ISOMETHYL-.ALPHA.-IONONE; DISODIUM EDTA-COPPER; BUTYLATED HYDROXYTOLUENE; PHENOXYETHANOL; POTASSIUM SORBATE; FERRIC OXIDE YELLOW; FERRIC OXIDE RED; FERROSOFERRIC OXIDE; MICA; WATER; PHENYL TRIMETHICONE; DIMETHICONE; PENTAERYTHRITYL TETRAISOSTEARATE; METHYL TRIMETHICONE; GLYCERIN; PROPANEDIOL; LAURYL PEG-9 POLYDIMETHYLSILOXYETHYL DIMETHICONE; SILICA, TRIMETHYLSILYL CAPPED; ISOHEXADECANE; CETYL PEG/PPG-10/1 DIMETHICONE (HLB 2); HYDROXYETHYL UREA; SAPINDUS MUKOROSSI FRUIT; HYALURONATE SODIUM; TREMELLA FUCIFORMIS FRUITING BODY; SOYBEAN; SACCHARINA LATISSIMA; LIMOSILACTOBACILLUS REUTERI; TREHALOSE; DIMETHICONE/VINYL DIMETHICONE CROSSPOLYMER (HARD PARTICLE); CAPRYLYL GLYCOL; DIISOSTEARYL MALATE; CAFFEINE; LINOLEIC ACID; PHOSPHOLIPID PHOSPHATASE 1; POLYGLYCERYL-2 TRIISOSTEARATE

ESTĒE LAUDER DOUBLE WEAR SOFT GLOW MATTE CUSHION MAKEUP BROAD SPECTRUM SPF 36

Drug Facts

ACTIVE INGREDIENT

Active ingredients | Purpose
Octinoxate 6.8% | Sunscreen
Titanium Dioxide 7.6% | Sunscreen
Zinc Oxide 3.6% | Sunscreen

Use

helps prevent sunburn

Warnings

For external use only

Do not use on damaged or broken skin

When using this product keep out of eyes. Rinse with water to remove.

Stop use and ask a doctor if rash occurs

Keep out of reach of children. If product is swallowed, get medical help or contact a Poison Control Center right away.

Directions

For sunscreen use:

- apply liberally 15 minutes before sun exposure
- reapply at least every two hours
- use a water resistant sunscreen if swimming or sweating
- Sun Protection Measures. Spending time in the sun increases your risk of skin cancer and early skin aging. To decrease this risk, regularly use a sunscreen with a Broad Spectrum SPF value of 15 or higher and other sun protection measures including:
  - limit time in the sun, especially from 10 a.m. – 2 p.m.
  - wear long-sleeved shirts, pants, hats and sunglasses
- children under 6 months of age: ask a doctor

Inactive ingredients

water\aqua\eau∙phenyl trimethicone∙dimethicone∙pentaerythrityl tetraisostearate∙methyl trimethicone∙glycerin∙propanediol∙lauryl peg-9 polydimethylsiloxyethyl dimethicone∙silica∙isohexadecane∙cetyl peg/ppg-10/1 dimethicone∙hydroxyethyl urea∙sapindus mukorossi fruit extract∙sodium hyaluronate∙tremella fuciformis sporocarp extract∙glycine soja (soybean) seed extract∙laminaria saccharina extract∙lactobacillus ferment∙trehalose∙dimethicone/vinyl dimethicone crosspolymer∙caprylyl glycol∙diisostearyl malate∙caffeine∙linoleic acid∙phospholipids∙polyglyceryl-2 triisostearate∙caprylic/capric triglyceride∙phytosteryl canola glycerides∙triolein∙tocopheryl acetate∙hydrogenated coco-glycerides∙methicone∙caesalpinia spinosa gum∙jojoba esters∙acetyl hexapeptide-8∙peg-75∙triethoxycaprylylsilane∙alumina∙disteardimonium hectorite∙propylene carbonate∙betaine∙dimethicone silylate∙tocopherol∙dimethicone/peg-10/15 crosspolymer∙magnesium sulfate∙palmitic acid∙oleic acid∙polymethylsilsesquioxane∙butylene glycol∙dipropylene glycol∙stearic acid∙polysilicone-11∙sodium citrate∙glyceryl stearate∙stearyl alcohol∙cetearyl alcohol∙ammonium polyacryloyldimethyl taurate∙polysorbate 80∙trimethylsiloxysilicate∙polysorbate 20∙behenyl alcohol∙dimethicone/divinyldimethicone silsesquioxane crosspolymer∙fragrance (parfum)∙linalool∙limonene∙alpha-isomethyl ionone∙disodium edta∙bht∙phenoxyethanol∙potassium sorbate∙[+/- titanium dioxide (ci 77891)∙iron oxides (ci 77492)∙iron oxides (ci 77491)∙iron oxides (ci 77499)∙mica] <iln49800>

Other information

protect the product in this container from excessive heat and direct sun

PRINCIPAL DISPLAY PANEL - 28 g Cartridge Carton

ESTĒE LAUDER

Double Wear
Soft Glow Matte
Cushion Makeup
Broad Spectrum SPF 36

Plus 1 Refill

TOTAL POIDS NET WT. .98 OZ./28g ℮ (14g X2)